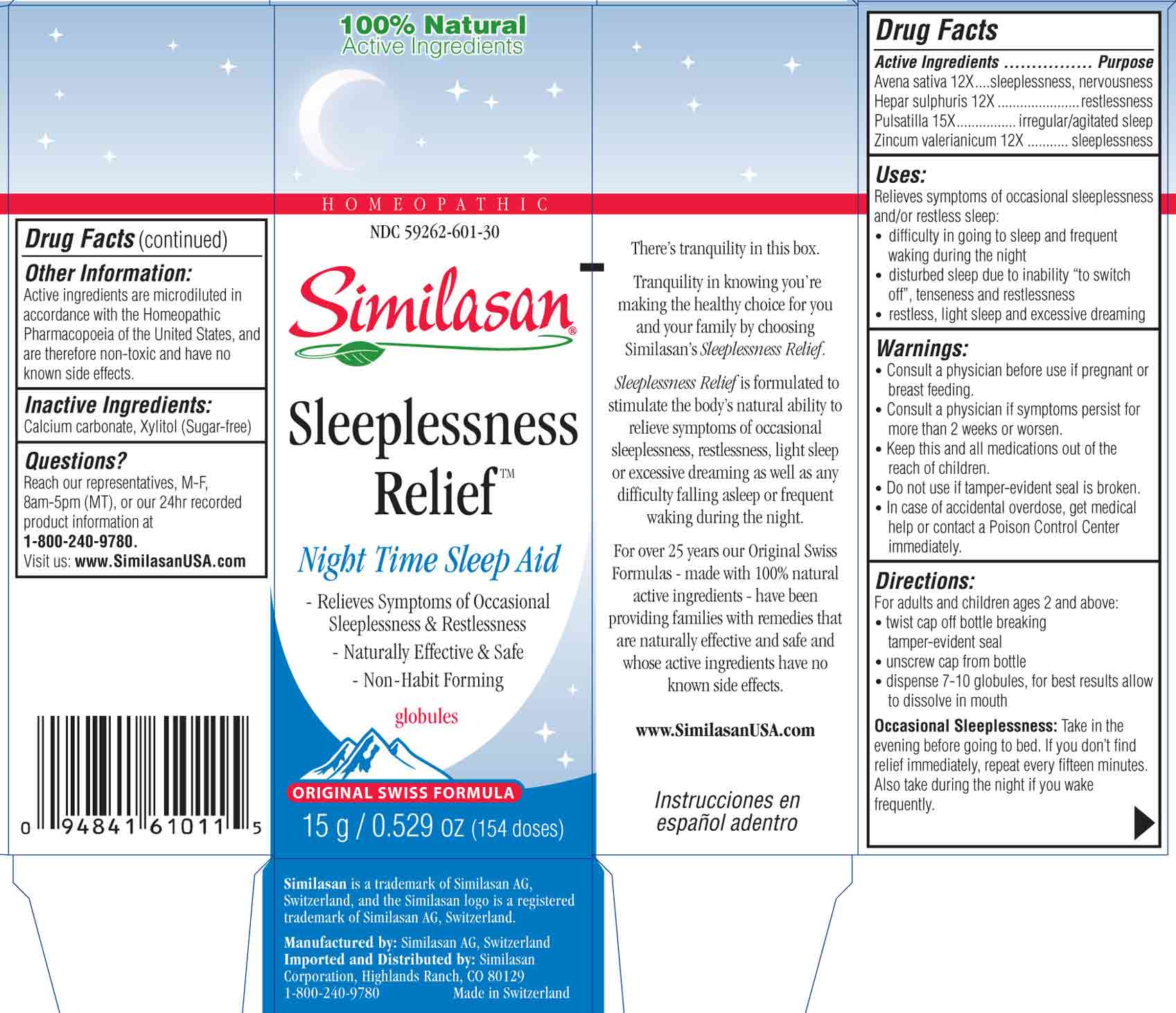 DRUG LABEL: Sleeplessness Relief
NDC: 59262-601 | Form: GLOBULE
Manufacturer: Similasan Corporation
Category: homeopathic | Type: HUMAN OTC DRUG LABEL
Date: 20130711

ACTIVE INGREDIENTS: AVENA SATIVA FLOWERING TOP 12 [hp_X]/1 1; CALCIUM SULFIDE 12 [hp_X]/1 1; ANEMONE PATENS 15 [hp_X]/1 1; ZINC VALERATE DIHYDRATE 12 [hp_X]/1 1
INACTIVE INGREDIENTS: CALCIUM CARBONATE; XYLITOL

Sleeplessness Relief

Active ingredient(s)

Avena sativa 12X

Purpose

sleeplessness, nervousness

Active ingredient(s)

Hepar sulphuris 12X

Purpose

restlessness

Active ingredient(s)

Pulsatilla 15X

Purpose

irregular/agitated sleep

Active ingredient(s)

Zincum valerianicum 12X

Purpose

sleeplessness

Uses:

Relieves symptoms of occasional sleeplessness and/or restless sleep
- Difficulty in going to sleep and frequent waking during the night
- Disturbed sleep due to inability "to switch off", tenseness and restlessness
- Restless, light sleep and excessive dreaming

Warnings:

- Consult a physician before use if pregnant or breast feeding.
- Consult a physician if symptoms persist for more than 2 weeks or worsen.
- Keep this and all medications out of the reach of children.
- Do not use if tamper-evident seal is broken.
- In case of accidental overdose, get medical help or contact a Poison Control Center immediately.

Keep out of reach of children

Keep this and all medications out of the reach of children

Directions:

For adults and children ages 2 and above:
- Remove tamper-evident seal from neck of bottle.
- Twist cap off bottle.
- Dispense 7-10 globules, place in mouth and allow to dissolve. Do not swallow globules.
- Allow the globules to dissolve in the mouth.

Occasional Sleeplessness: Take in the evening before going to bed. If you don't find relief immediately, repeat every fifteen minutes. Also take during the night if you wake frequently.

Other information:

Active ingredients are microdiluted in accordance with the Homeopathic Pharmacopoeia of the United States, and are therefore non-toxic and have no known side effects.

Inactive ingredients:

Calcium carbonate, Xylitol (Sugar-free)

Questions?

Call 1-800-240-9780 for 24hr recorded product information. Representatives available, M-F, 8am-5pm (MT), or visit: www.SimilasanUSA.com

Principal Display Panel

NDC 59262-601-30
Similasan
Sleeplessness Relief
Globules
15g/ 0.529 oz
Sleeplessness Relief Box